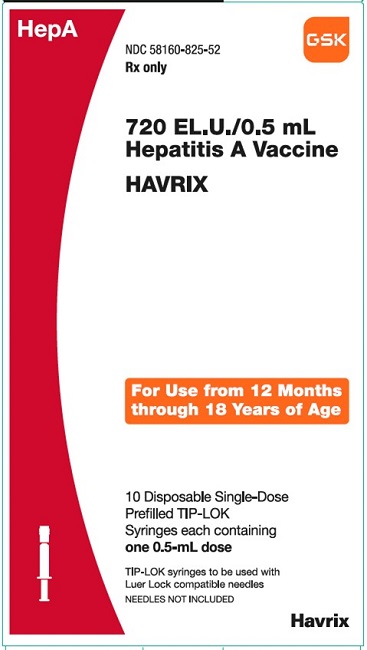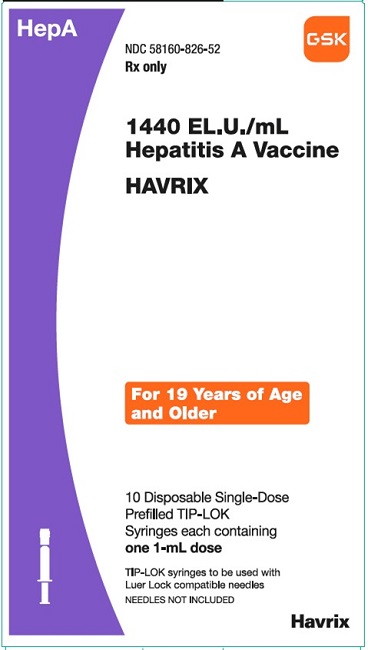 DRUG LABEL: HAVRIX
NDC: 58160-825 | Form: INJECTION, SUSPENSION
Manufacturer: GlaxoSmithKline Biologicals SA
Category: other | Type: VACCINE LABEL
Date: 20241218

ACTIVE INGREDIENTS: HEPATITIS A VIRUS STRAIN HM175 ANTIGEN (FORMALDEHYDE INACTIVATED) 720 [iU]/0.5 mL
INACTIVE INGREDIENTS: ALUMINUM HYDROXIDE; POLYSORBATE 20

HIGHLIGHTS OF PRESCRIBING INFORMATION

These highlights do not include all the information needed to use HAVRIX safely and effectively. See full prescribing information for HAVRIX.
HAVRIX (Hepatitis A Vaccine) injectable suspension, for intramuscular use
Initial U.S. Approval: 1995

1 INDICATIONS AND USAGE

HAVRIX is a vaccine indicated for active immunization against disease caused by hepatitis A virus (HAV). HAVRIX is approved for use in persons 12 months of age and older. Primary immunization should be administered at least 2 weeks prior to expected exposure to HAV. (1)

2 DOSAGE AND ADMINISTRATION

- HAVRIX is administered by intramuscular injection. (2.2)
- Children and adolescents: A single 0.5-mL dose and a 0.5-mL booster dose administered between 6 to 12 months later. (2.3)
- Adults: A single 1-mL dose and a 1-mL booster dose administered between 6 to 12 months later. (2.3)

3 DOSAGE FORMS AND STRENGTHS

- Suspension for injection available in the following presentations:
- 0.5-mL single-dose prefilled syringes. (3)
- 1-mL single-dose prefilled syringes. (3)

4 CONTRAINDICATIONS

Severe allergic reaction (e.g., anaphylaxis) after a previous dose of any hepatitis A-containing vaccine, or to any component of HAVRIX, including neomycin. (4)

5 WARNINGS AND PRECAUTIONS

Syncope (fainting) can occur in association with administration of injectable vaccines, including HAVRIX. Procedures should be in place to avoid falling injury and to restore cerebral perfusion following syncope. (5.1)

6 ADVERSE REACTIONS

- In studies of adults and children 2 years of age and older, the most common solicited adverse reactions were injection-site soreness (56% of adults and 21% of children) and headache (14% of adults and less than 9% of children). (6.1)
- In studies of children 11 to 25 months of age, the most frequently reported solicited local reactions were pain (32%) and redness (29%). Common solicited general adverse reactions were irritability (42%), drowsiness (28%), and loss of appetite (28%). (6.1)

To report SUSPECTED ADVERSE REACTIONS, contact GlaxoSmithKline at 1-888-825-5249 or VAERS at 1-800-822-7967 or www.vaers.hhs.gov.

7 DRUG INTERACTIONS

Do not mix HAVRIX with any other vaccine or product in the same syringe. (7.1)

FULL PRESCRIBING INFORMATION

1 INDICATIONS AND USAGE

HAVRIX is indicated for active immunization against disease caused by hepatitis A virus (HAV). HAVRIX is approved for use in persons 12 months of age and older. Primary immunization should be administered at least 2 weeks prior to expected exposure to HAV.

2 DOSAGE AND ADMINISTRATION

2.1 Preparation for Administration

Shake well before use. With thorough agitation, HAVRIX is a homogeneous, turbid, white suspension. Do not administer if it appears otherwise. Parenteral drug products should be inspected visually for particulate matter and discoloration prior to administration, whenever solution and container permit. If either of these conditions exists, the vaccine should not be administered. Attach a sterile needle to the prefilled syringe and administer intramuscularly.

2.2 Administration

HAVRIX should be administered by intramuscular injection only. HAVRIX should not be administered in the gluteal region; such injections may result in suboptimal response.

Do not administer this product intravenously, intradermally, or subcutaneously.

2.3 Recommended Dose and Schedule

Children and Adolescents (aged 12 months through 18 years)

Primary immunization for children and adolescents consists of a single 0.5-mL dose and a 0.5-mL booster dose administered anytime between 6 and 12 months later. The preferred sites for intramuscular injections are the anterolateral aspect of the thigh in young children or the deltoid muscle of the upper arm in older children.

Adults (aged 19 years and older)

Primary immunization for adults consists of a single 1-mL dose and a 1-mL booster dose administered anytime between 6 and 12 months later. In adults, the injection should be given in the deltoid region.

3 DOSAGE FORMS AND STRENGTHS

Suspension for injection available in the following presentations:

- 0.5-mL single-dose prefilled TIP-LOK syringes.
- 1-mL single-dose prefilled TIP-LOK syringes. [See How Supplied/Storage and Handling (16).]

4 CONTRAINDICATIONS

Severe allergic reaction (e.g., anaphylaxis) after a previous dose of any hepatitis A-containing vaccine, or to any component of HAVRIX, including neomycin, is a contraindication to administration of HAVRIX [see Description (11)].

5 WARNINGS AND PRECAUTIONS

5.1 Syncope

Syncope (fainting) can occur in association with administration of injectable vaccines, including HAVRIX. Syncope can be accompanied by transient neurological signs such as visual disturbance, paresthesia, and tonic-clonic limb movements. Procedures should be in place to avoid falling injury and to restore cerebral perfusion following syncope.

5.2 Preventing and Managing Allergic Vaccine Reactions

Appropriate medical treatment and supervision must be available to manage possible anaphylactic reactions following administration of the vaccine [see Contraindications (4)].

5.3 Altered Immunocompetence

Immunocompromised persons may have a diminished immune response to HAVRIX, including individuals receiving immunosuppressant therapy.

5.4 Limitations of Vaccine Effectiveness

Hepatitis A virus has a relatively long incubation period (15 to 50 days). HAVRIX may not prevent hepatitis A infection in individuals who have an unrecognized hepatitis A infection at the time of vaccination. Additionally, vaccination with HAVRIX may not protect all individuals.

6 ADVERSE REACTIONS

6.1 Clinical Trials Experience

Because clinical trials are conducted under widely varying conditions, adverse reaction rates observed in the clinical trials of a vaccine cannot be directly compared with rates in the clinical trials of another vaccine and may not reflect the rates observed in practice.

The safety of HAVRIX has been evaluated in 61 clinical trials involving approximately 37,000 individuals receiving doses of 360 EL.U. (n = 21,928 in 3- or 4-dose schedule), 720 EL.U. (n = 12,274 in 2- or 3-dose schedule), or 1440 EL.U. (n = 2,782 in 2- or 3-dose schedule).

Of solicited adverse reactions in clinical trials of adults, who received HAVRIX 1440 EL.U., and children (aged 2 years and older), who received either HAVRIX 360 EL.U. or 720 EL.U., the most frequently reported was injection-site soreness (56% of adults and 21% of children); less than 0.5% of soreness was reported as severe. Headache was reported by 14% of adults and less than 9% of children. Other solicited and unsolicited reactions occurring during clinical trials are listed below.

Incidence 1% to 10% of Injections

Metabolism and Nutrition Disorders: Anorexia.

Gastrointestinal Disorders: Nausea.

General Disorders and Administration Site Conditions: Fatigue; fever >99.5°F (37.5°C); induration, redness, and swelling of the injection site; malaise.

Incidence <1% of Injections

Infections and Infestations: Pharyngitis, upper respiratory tract infections.

Blood and Lymphatic System Disorders: Lymphadenopathy.

Psychiatric Disorders: Insomnia.

Nervous System Disorders: Dysgeusia, hypertonia.

Eye Disorders: Photophobia.

Ear and Labyrinth Disorders: Vertigo.

Gastrointestinal Disorders: Abdominal pain, diarrhea, vomiting.

Skin and Subcutaneous Tissue Disorders: Pruritus, rash, urticaria.

Musculoskeletal and Connective Tissue Disorders: Arthralgia, myalgia.

General Disorders and Administration Site Conditions: Injection site hematoma.

Investigations: Creatine phosphokinase increased.

Coadministration Studies of HAVRIX in Children Aged 11 to 25 Months

In 4 studies, 3,152 children aged 11 to 25 months received at least 1 dose of HAVRIX 720 EL.U. administered alone or concomitantly with other routine childhood vaccinations [see Clinical Studies (14.2, 14.5)]. The studies included HAV 210 (N = 1,084), HAV 232 (N = 394), HAV 220 (N = 433), and HAV 231 (N = 1,241).

In the largest of these studies (HAV 231) conducted in the U.S., 1,241 children aged 15 months were randomized to receive: Group 1) HAVRIX alone; Group 2) HAVRIX concomitantly with measles, mumps, and rubella (MMR) vaccine (manufactured by Merck and Co.) and varicella vaccine (manufactured by Merck and Co.); or Group 3) MMR and varicella vaccines. Subjects in Group 3 who received MMR and varicella vaccines received the first dose of HAVRIX 42 days later. A second dose of HAVRIX was administered to all subjects 6 to 9 months after the first dose of HAVRIX. Solicited local adverse reactions and general events were recorded by parents/guardians on diary cards for 4 days (Days 0 to 3) after vaccination. Unsolicited adverse events were recorded on the diary card for 31 days after vaccination. Telephone follow-up was conducted 6 months after the last vaccination to inquire about serious adverse events, new onset chronic illnesses, and medically significant events. A total of 1,035 children completed the 6-month follow-up. Among subjects in all groups combined, 53% were male; 69% of subjects were White, 16% were Hispanic, 9% were Black, and 6% were other racial/ethnic groups.

Percentages of subjects with solicited local adverse reactions and general adverse reactions following HAVRIX administered alone (Group 1) or concomitantly with MMR and varicella vaccines (Group 2) are presented in Table 1. The solicited adverse reactions from the 3 additional coadministration studies conducted with HAVRIX were comparable to those from Study HAV 231.

Table 1. Solicited Local Adverse Reactions and General Adverse Reactions Occurring within 4 Days of Vaccinationa in Children Aged 15 to 24 Months with HAVRIX Administered Alone or Concomitantly with MMR and Varicella Vaccines (TVC)
 | Group 1; HAVRIX; Dose 1; % | Group 2; HAVRIX+; MMR+Vb; Dose 1; % | Group 1; HAVRIX; Dose 2; % | Group 2; HAVRIX; Dose 2; %
Local (at injection site for HAVRIX)
n | 298 | 411 | 272 | 373
Pain, any | 24 | 24 | 24 | 30
Redness, any | 20 | 20 | 23 | 24
Swelling, any | 9 | 10 | 10 | 10
General
n | 300 | 417 | 271 | 375
Irritability, any | 33 | 44 | 31 | 27
Irritability, Grade 3 | 0 | 2 | 2 | 0
Drowsiness, any | 22 | 35 | 21 | 21
Drowsiness, Grade 3 | 1 | 2 | 1 | 0
Loss of appetite, any | 18 | 26 | 20 | 21
Loss of appetite, Grade 3 | 1 | 1 | 0 | 0
Fever ≥100.6°F (38.1°C) | 3 | 5 | 3 | 3
Fever ≥101.5°F (38.6°C) | 2 | 3 | 2 | 2
Fever ≥102.4°F (39.1°C) | 1 | 1 | 0 | 1
Total vaccinated cohort (TVC) = all subjects who received at least 1 dose of vaccine.
n = Number of subjects who received at least 1 dose of vaccine and for whom diary card information was available.
Grade 3: Drowsiness defined as prevented normal daily activities; irritability/fussiness defined as crying that could not be comforted/prevented normal daily activities; loss of appetite defined as no eating at all.
a Within 4 days of vaccination defined as day of vaccination and the next 3 days.
b MMR = Measles, mumps, and rubella vaccine; V = Varicella vaccine.

Serious Adverse Events in Children Aged 11 to 25 Months: Among these 4 studies, 0.9% (29/3,152) of subjects reported a serious adverse event within the 31-day period following vaccination with HAVRIX. Among subjects administered HAVRIX alone 1.0% (13/1,332) reported a serious adverse event. Among subjects who received HAVRIX concomitantly with other childhood vaccines, 0.9% (8/909) reported a serious adverse event. In these 4 studies, there were 4 reports of seizure within 31 days post-vaccination: these occurred 2, 9, and 27 days following the first dose of HAVRIX administered alone and 12 days following the second dose of HAVRIX. In 1 subject who received INFANRIX (Diphtheria and Tetanus Toxoids and Acellular Pertussis Vaccine Adsorbed) and Hib conjugate vaccine followed by HAVRIX 6 weeks later, bronchial hyperreactivity and respiratory distress were reported on the day of administration of HAVRIX alone.

6.2 Postmarketing Experience

The following adverse reactions have been identified during post-approval use of HAVRIX. Because these reactions are reported voluntarily from a population of uncertain size, it is not always possible to reliably estimate their frequency or establish a causal relationship to the vaccine.

Infections and Infestations

Rhinitis.

Blood and Lymphatic System Disorders

Thrombocytopenia.

Immune System Disorders

Anaphylactic reaction, anaphylactoid reaction, serum sickness–like syndrome.

Nervous System Disorders

Convulsion, dizziness, encephalopathy, Guillain-Barré syndrome, hypoesthesia, multiple sclerosis, myelitis, neuropathy, paresthesia, somnolence, syncope.

Vascular Disorders

Vasculitis.

Respiratory, Thoracic, and Mediastinal Disorders

Dyspnea.

Hepatobiliary Disorders

Hepatitis, jaundice.

Skin and Subcutaneous Tissue Disorders

Angioedema, erythema multiforme, hyperhidrosis.

Congenital, Familial, and Genetic Disorders

Congenital anomaly.

Musculoskeletal and Connective Tissue Disorders

Musculoskeletal stiffness.

General Disorders and Administration Site Conditions

Chills, influenza-like symptoms, injection site reaction, local swelling.

7 DRUG INTERACTIONS

7.1 Concomitant Administration with Vaccines and Immune Globulin

In clinical studies HAVRIX was administered concomitantly with the following vaccines [see Adverse Reactions (6.1), Clinical Studies (14.5)].

- INFANRIX (DTaP);
- Hib conjugate vaccine;
- pneumococcal 7-valent conjugate vaccine;
- MMR vaccine;
- varicella vaccine.

HAVRIX may be administered concomitantly with immune globulin.

When concomitant administration of other vaccines or immune globulin is required, they should be given with different syringes and at different injection sites. Do not mix HAVRIX with any other vaccine or product in the same syringe.

7.2 Immunosuppressive Therapies

Immunosuppressive therapies, including irradiation, antimetabolites, alkylating agents, cytotoxic drugs, and corticosteroids (used in greater-than-physiologic doses), may reduce the immune response to HAVRIX.

8 USE IN SPECIFIC POPULATIONS

8.1 Pregnancy

Risk Summary

All pregnancies have a risk of birth defect, loss, or other adverse outcomes. In the U.S. general population, the estimated background risk of major birth defects and miscarriage in clinically recognized pregnancies is 2% to 4% and 15% to 20%, respectively.

There are no adequate and well-controlled studies of HAVRIX in pregnant women in the U.S. Available data do not suggest an increased risk of major birth defects and miscarriage in women who received HAVRIX during pregnancy (see Data).

There are no animal studies with HAVRIX to inform use during pregnancy.

Data

Human Data: In pre- and post-licensure clinical studies of HAVRIX, 175 pregnant women (177 outcomes, including two sets of twins) were inadvertently administered HAVRIX following their last menstrual period. After excluding ectopic pregnancies (n = 2), molar pregnancies (n = 1), elective terminations (n = 22, including one of a fetus with a birth defect), those that were lost to follow-up (n = 9), and those with an unknown exposure timing (n = 5), there were 138 known pregnancy outcomes with exposure during the first or second trimester. Of these, miscarriage was reported in 11% of pregnancies exposed prior to 20 weeks gestation (15/136) and major birth defects were reported in 3.3% (4/123) of live births. The rates of miscarriage and major birth defects were consistent with estimated background rates.

8.2 Lactation

Risk Summary

There is no information regarding the presence of HAVRIX in human milk, the effects on the breastfed child, or the effects on milk production. The developmental and health benefits of breastfeeding should be considered along with the mother’s clinical need for HAVRIX and any potential adverse effects on the breastfed child from HAVRIX or from the underlying maternal condition. For preventive vaccines, the underlying maternal condition is susceptibility to disease prevented by the vaccine.

8.4 Pediatric Use

The safety and effectiveness of HAVRIX, doses of 360 EL.U. or 720 EL.U., have been evaluated in more than 22,000 subjects aged 1 to 18 years.

The safety and effectiveness of HAVRIX have not been established in subjects younger than 12 months.

8.5 Geriatric Use

Clinical studies of HAVRIX did not include sufficient numbers of subjects aged 65 years and older to determine whether they respond differently from younger subjects. Other reported clinical experience has not identified differences in overall safety between these subjects and younger adult subjects.

8.6 Hepatic Impairment

Subjects with chronic liver disease had a lower antibody response to HAVRIX than healthy subjects [see Clinical Studies (14.3)].

11 DESCRIPTION

HAVRIX (Hepatitis A Vaccine) is a sterile suspension of inactivated virus for intramuscular administration. The virus (strain HM175) is propagated in MRC-5 human diploid cells. After removal of the cell culture medium, the cells are lysed to form a suspension. This suspension is purified through ultrafiltration and gel permeation chromatography procedures. Treatment of this lysate with formalin ensures viral inactivation. Viral antigen activity is referenced to a standard using an enzyme linked immunosorbent assay (ELISA), and is therefore expressed in terms of ELISA Units (EL.U.).

Each 1-mL adult dose of vaccine contains 1440 EL.U. of viral antigen, adsorbed on 0.5 mg of aluminum as aluminum hydroxide.

Each 0.5-mL pediatric dose of vaccine contains 720 EL.U. of viral antigen, adsorbed onto 0.25 mg of aluminum as aluminum hydroxide.

HAVRIX contains the following excipients: Amino acid supplement (0.3% w/v) in a phosphate-buffered saline solution and polysorbate 20 (0.05 mg/mL). From the manufacturing process, HAVRIX also contains residual MRC-5 cellular proteins (not more than 5 mcg/mL), formalin (not more than 0.1 mg/mL), and neomycin sulfate (not more than 40 ng/mL), an aminoglycoside antibiotic included in the cell growth media.

HAVRIX is formulated without preservatives.

HAVRIX is available in prefilled syringes. The tip cap and rubber plunger stopper of the prefilled syringe are not made with natural rubber latex.

12 CLINICAL PHARMACOLOGY

12.1 Mechanism of Action

The hepatitis A virus belongs to the picornavirus family. It is 1 of several hepatitis viruses that cause systemic disease with pathology in the liver.

The incubation period for hepatitis A averages 28 days (range: 15 to 50 days).^1 The course of hepatitis A infection is extremely variable, ranging from asymptomatic infection to icteric hepatitis and death.

The presence of antibodies to HAV confers protection against hepatitis A infection. However, the lowest titer needed to confer protection has not been determined.

13 NONCLINICAL TOXICOLOGY

13.1 Carcinogenesis, Mutagenesis, Impairment of Fertility

HAVRIX has not been evaluated for its carcinogenic potential, mutagenic potential, or potential for impairment of fertility.

14 CLINICAL STUDIES

14.1 Pediatric Effectiveness Studies

Protective efficacy with HAVRIX has been demonstrated in a double-blind, randomized controlled study in school children (aged 1 to 16 years) in Thailand who were at high risk of HAV infection. A total of 40,119 children were randomized to be vaccinated with either HAVRIX 360 EL.U. or ENGERIX-B [Hepatitis B Vaccine (Recombinant)] 10 mcg at 0, 1, and 12 months. Of these, 19,037 children received 2 doses of HAVRIX (0 and 1 months) and 19,120 children received 2 doses of control vaccine, ENGERIX-B (0 and 1 months). A total of 38,157 children entered surveillance at Day 138 and were observed for an additional 8 months. Using the protocol-defined endpoint (≥2 days absence from school, ALT level >45 U/mL, and a positive result in the HAVAB-M test), 32 cases of clinical hepatitis A occurred in the control group. In the group receiving HAVRIX, 2 cases were identified. These 2 cases were mild in terms of both biochemical and clinical indices of hepatitis A disease. Thus the calculated efficacy rate for prevention of clinical hepatitis A was 94% (95% Confidence Interval [CI]: 74, 98).

In outbreak investigations occurring in the trial, 26 clinical cases of hepatitis A (of a total of 34 occurring in the trial) occurred. No cases occurred in vaccinees who received HAVRIX.

Using additional virological and serological analyses post hoc, the efficacy of HAVRIX was confirmed. Up to 3 additional cases of mild clinical illness may have occurred in vaccinees. Using available testing, these illnesses could neither be proven nor disproven to have been caused by HAV. By including these as cases, the calculated efficacy rate for prevention of clinical hepatitis A would be 84% (95% CI: 60, 94).

14.2 Immunogenicity in Children and Adolescents

Immune Response to HAVRIX 720 EL.U./0.5 mL at Age 11 to 25 Months (Study HAV 210)

In this prospective, open-label, multicenter study, 1,084 children were administered study vaccine in 1 of 5 groups:

(1) Children aged 11 to 13 months who received HAVRIX on a 0- and 6-month schedule;

(2) Children aged 15 to 18 months who received HAVRIX on a 0- and 6-month schedule;

(3) Children aged 15 to 18 months who received HAVRIX coadministered with INFANRIX and Haemophilus b (Hib) conjugate vaccine (no longer U.S.-licensed) at Month 0 and HAVRIX at Month 6;

(4) Children aged 15 to 18 months who received INFANRIX coadministered with Hib conjugate vaccine at Month 0 and HAVRIX at Months 1 and 7;

(5) Children aged 23 to 25 months who received HAVRIX on a 0- and 6-month schedule.

Among subjects in all groups, 52% were male; 61% of subjects were White, 9% were Black, 3% were Asian, and 27% were other racial/ethnic groups. The anti-hepatitis A antibody vaccine responses and geometric mean antibody titers (GMTs), calculated on responders for Groups 1, 2, and 5 are presented in Table 2. Vaccine response rates were similar among the 3 age-groups that received HAVRIX. One month after the second dose of HAVRIX, the GMT in each of the younger age-groups (aged 11 to 13 months and 15 to 18 months) was shown to be similar to that achieved in the 23- to 25-month age-group.

Table 2. Anti-Hepatitis A Immune Response following 2 Doses of HAVRIX 720 EL.U./0.5 mL Administered 6 Months Apart in Children Given the First Dose of HAVRIX at Age 11 to 13 Months, 15 to 18 Months, or 23 to 25 Months
Age Group | n | Vaccine Response |  | GMT; (mIU/mL)
Age Group | n | % | 95% CI | GMT; (mIU/mL)
11-13 months (Group 1) | 218 | 99 | 97, 100 | 1,461a
15-18 months (Group 2) | 200 | 100 | 98, 100 | 1,635a
23-25 months (Group 5) | 211 | 100 | 98, 100 | 1,911
Vaccine response = Seroconversion (anti-HAV ≥15 mIU/mL [lower limit of antibody measurement by assay]) in children initially seronegative or at least the maintenance of the pre-vaccination anti-HAV concentration in initially seropositive children.
CI = Confidence Interval; GMT = Geometric mean antibody titer.
a Calculated on vaccine responders 1 month post-dose 2. GMTs in children aged 11 to 13 months and 15 to 18 months were non-inferior (similar) to the GMT in children aged 23 to 25 months (i.e., the lower limit of the 2-sided 95% CI on the GMT ratio for Group 1/Group 5 and for Group 2/Group 5 were both ≥0.5).

In 3 additional clinical studies (HAV 232, HAV 220, and HAV 231), children received either 2 doses of HAVRIX alone or the first dose of HAVRIX concomitantly administered with other routinely recommended U.S.-licensed vaccines followed by a second dose of HAVRIX. After the second dose of HAVRIX, there was no evidence for interference with the anti-HAV response in the children who received concomitantly administered vaccines compared with those who received HAVRIX alone. [See Adverse Reactions (6.1), Clinical Studies (14.5).]

Immune Response to HAVRIX 360 EL.U. among Individuals Aged 2 to 18 Years

In 6 clinical studies, 762 subjects aged 2 to 18 years received 2 doses of HAVRIX (360 EL.U.) given 1 month apart (GMT ranged from 197 to 660 mIU/mL). Ninety-nine percent of subjects seroconverted following 2 doses. When a third dose of HAVRIX 360 EL.U. was administered 6 months following the initial dose, all subjects were seropositive (anti-HAV ≥20 mIU/mL) 1 month following the third dose, with GMTs rising to a range of 3,388 to 4,643 mIU/mL. In 1 study in which children were followed for an additional 6 months, all subjects remained seropositive.

Immune Response to HAVRIX 720 EL.U./0.5 mL among Individuals Aged 2 to 19 Years

In 4 clinical studies, 314 children and adolescents ranging from age 2 to 19 years were immunized with 2 doses of HAVRIX 720 EL.U./0.5 mL given 6 months apart. One month after the first dose, seroconversion (anti-HAV ≥20 mIU/mL [lower limit of antibody measurement by assay]) ranged from 96.8% to 100%, with GMTs of 194 mIU/mL to 305 mIU/mL. In studies in which sera were obtained 2 weeks following the initial dose, seroconversion ranged from 91.6% to 96.1%. One month following the booster dose at Month 6, all subjects were seropositive, with GMTs ranging from 2,495 mIU/mL to 3,644 mIU/mL.

In an additional study in which the booster dose was delayed until 1 year following the initial dose, 95.2% of the subjects were seropositive just prior to administration of the booster dose. One month later, all subjects were seropositive, with a GMT of 2,657 mIU/mL.

14.3 Immunogenicity in Adults

More than 400 healthy adults aged 18 to 50 years in 3 clinical studies were given a single 1440 EL.U. dose of HAVRIX. All subjects were seronegative for hepatitis A antibodies at baseline. Specific humoral antibodies against HAV were elicited in more than 96% of subjects when measured 1 month after vaccination. By Day 15, 80% to 98% of vaccinees had already seroconverted (anti-HAV ≥20 mIU/mL [lower limit of antibody measurement by assay]). GMTs of seroconverters ranged from 264 to 339 mIU/mL at Day 15 and increased to a range of 335 to 637 mIU/mL by 1 month following vaccination.

The GMTs obtained following a single dose of HAVRIX are at least several times higher than that expected following receipt of immune globulin.

In a clinical study using 2.5 to 5 times the standard dose of immune globulin (standard dose = 0.02 to 0.06 mL/kg), the GMT in recipients was 146 mIU/mL at 5 days post-administration, 77 mIU/mL at Month 1, and 63 mIU/mL at Month 2.

In 2 clinical trials in which a booster dose of 1440 EL.U. was given 6 months following the initial dose, 100% of vaccinees (n = 269) were seropositive 1 month after the booster dose, with GMTs ranging from 3,318 mIU/mL to 5,925 mIU/mL. The titers obtained from this additional dose approximate those observed several years after natural infection.

In a subset of vaccinees (n = 89), a single dose of HAVRIX 1440 EL.U. elicited specific anti-HAV neutralizing antibodies in more than 94% of vaccinees when measured 1 month after vaccination. These neutralizing antibodies persisted until Month 6. One hundred percent of vaccinees had neutralizing antibodies when measured 1 month after a booster dose given at Month 6.

Immunogenicity of HAVRIX was studied in subjects with chronic liver disease of various etiologies. One hundred eighty-nine healthy adults and 220 adults with either chronic hepatitis B (n = 46), chronic hepatitis C (n = 104), or moderate chronic liver disease of other etiology (n = 70) were vaccinated with HAVRIX 1440 EL.U. on a 0- and 6-month schedule. The last group consisted of alcoholic cirrhosis (n = 17), autoimmune hepatitis (n = 10), chronic hepatitis/cryptogenic cirrhosis (n = 9), hemochromatosis (n = 2), primary biliary cirrhosis (n = 15), primary sclerosing cholangitis (n = 4), and unspecified (n = 13). At each time point, GMTs were lower for subjects with chronic liver disease than for healthy subjects. At Month 7, the GMTs ranged from 478 mIU/mL (chronic hepatitis C) to 1,245 mIU/mL (healthy). One month after the first dose, seroconversion rates in adults with chronic liver disease were lower than in healthy adults. However, 1 month after the booster dose at Month 6, seroconversion rates were similar in all groups; rates ranged from 94.7% to 98.1%. The relevance of these data to the duration of protection afforded by HAVRIX is unknown.

In subjects with chronic liver disease, local injection site reactions with HAVRIX were similar among all 4 groups, and no serious adverse reactions attributed to the vaccine were reported in subjects with chronic liver disease.

14.4 Duration of Immunity

The duration of immunity following a complete schedule of immunization with HAVRIX has not been established.

14.5 Immune Response to Concomitantly Administered Vaccines

In 3 clinical studies HAVRIX was administered concomitantly with other routinely recommended U.S.-licensed vaccines: Study HAV 232: Diphtheria and tetanus toxoids and acellular pertussis vaccine adsorbed (INFANRIX, DTaP) and Haemophilus b (Hib) conjugate vaccine (tetanus toxoid conjugate) (manufactured by Sanofi Pasteur SA); Study HAV 220: Pneumococcal 7-valent conjugate vaccine (PCV-7) (manufactured by Pfizer), and Study HAV 231: MMR and varicella vaccines. [See Adverse Reactions (6.1).]

Concomitant Administration with DTaP and Hib Conjugate Vaccine (Study HAV 232)

In this U.S. multicenter study, 468 subjects, children aged 15 months were randomized to receive: Group 1) HAVRIX coadministered with INFANRIX and Hib conjugate vaccine (n = 127); Group 2) INFANRIX and Hib conjugate vaccine alone followed by a first dose of HAVRIX 1 month later (n = 132); or Group 3) HAVRIX alone (n = 135). All subjects received a second dose of HAVRIX alone 6 to 9 months following the first dose. Among subjects in all groups combined, 53% were male; 64% of subjects were White, 12% were Black, 6% were Hispanic, and 18% were other racial/ethnic groups.

There was no evidence for reduced antibody response to diphtheria and tetanus toxoids (percentage of subjects with antibody levels ≥0.1 mIU/mL to each antigen), pertussis antigens (percentage of subjects with seroresponse, antibody concentrations ≥5 EL.U./mL in seronegative subjects or post-vaccination antibody concentration ≥2 times the pre-vaccination antibody concentration in seropositive subjects, and GMTs), or Hib (percentage of subjects with antibody levels ≥1 mcg/mL to polyribosyl-ribitol phosphate, PRP) when HAVRIX was administered concomitantly with INFANRIX and Hib conjugate vaccine (Group 1) relative to INFANRIX and Hib conjugate vaccine administered together (Group 2).

Concomitant Administration with Pneumococcal 7-Valent Conjugate Vaccine (Study HAV 220)

In this U.S. multicenter study, 433 children aged 15 months were randomized to receive: Group 1) HAVRIX coadministered with PCV-7 vaccine (n = 137); Group 2) HAVRIX administered alone (n = 147); or Group 3) PCV-7 vaccine administered alone (n = 149) followed by a first dose of HAVRIX 1 month later. All subjects received a second dose of HAVRIX 6 to 9 months after the first dose. Among subjects in all groups combined, 53% were female; 61% of subjects were White, 16% were Hispanic, 15% were Black, and 8% were other racial/ethnic groups.

There was no evidence for reduced antibody response to PCV-7 (GMC to each serotype) when HAVRIX was administered concomitantly with PCV-7 vaccine (Group 1) relative to PCV-7 administered alone (Group 3).

Concomitant Administration with MMR and Varicella Vaccines (Study HAV 231)

In a U.S. multicenter study, there was no evidence for interference in the immune response to MMR and varicella vaccines (the percentage of subjects with pre-specified seroconversion/seroresponse levels) administered to subjects aged 15 months concomitantly with HAVRIX relative to the response when MMR and varicella vaccines are administered without HAVRIX. [See Adverse Reactions (6.1).]

15 REFERENCES

1. Centers for Disease Control and Prevention. Prevention of hepatitis A through active or passive immunization: Recommendations of the Immunization Practices Advisory Committee (ACIP). MMWR. 2006;55(RR-7):1-23.

16 HOW SUPPLIED/STORAGE AND HANDLING

HAVRIX is available in single-dose prefilled disposable TIP-LOK syringes (Luer Lock syringes) packaged without needles (Preservative-Free Formulation). TIP-LOK syringes are to be used with Luer Lock compatible needles. The tip cap and rubber plunger stopper of the prefilled syringe are not made with natural rubber latex.

720 EL.U./0.5 mL

NDC 58160-825-43 Prefilled Syringe in Package of 10: NDC 58160-825-52

1440 EL.U./mL

NDC 58160-826-43 Prefilled Syringe in Package of 10: NDC 58160-826-52

Store refrigerated between 2° and 8°C (36° and 46°F). Do not freeze. Discard if the vaccine has been frozen. Do not dilute to administer.

17 PATIENT COUNSELING INFORMATION

- Inform vaccine recipients and parents or guardians of the potential benefits and risks of immunization with HAVRIX.
- Emphasize, when educating vaccine recipients and parents or guardians regarding potential side effects, that HAVRIX contains non-infectious killed viruses and cannot cause hepatitis A infection.
- Instruct vaccine recipients and parents or guardians to report any adverse events to their healthcare provider.
- Give vaccine recipients and parents or guardians the Vaccine Information Statements, which are required by the National Childhood Vaccine Injury Act of 1986 to be given prior to immunization. These materials are available free of charge at the Centers for Disease Control and Prevention (CDC) website (www.cdc.gov/vaccines).

HAVRIX, ENGERIX-B, INFANRIX, AND TIP-LOK are trademarks owned by or licensed to the GSK group of companies.

Manufactured by GlaxoSmithKline Biologicals

Rixensart, Belgium, U.S. License No. 1617

Distributed by GlaxoSmithKline

Durham, NC 27701

©2024 GSK group of companies or its licensor.

HVX:49PI

PACKAGE LABEL

PRINCIPAL DISPLAY PANEL

NDC 58160-825-52

HAVRIX

720 EL.U./0.5 mL

Hepatitis A Vaccine

HepA

Rx only

For Use from 12 Months through 18 Years of Age

10 Disposable Single-Dose Prefilled TIP-LOK Syringes each containing one 0.5-mL dose

TIP-LOK syringes to be used with Luer Lock compatible needles

NEEDLES NOT INCLUDED

GSK

Havrix

Made in Belgium

©2023 GSK group of companies or its licensor.

Rev.10/23

515876

PACKAGE LABEL

PRINCIPAL DISPLAY PANEL

NDC 58160-826-52

HAVRIX

1440 EL.U./mL

Hepatitis A Vaccine

HepA

Rx only

For 19 Years of Age and Older

10 Disposable Single-Dose Prefilled TIP-LOK Syringes each containing one 1-mL dose

TIP-LOK syringes to be used with Luer Lock compatible needles

NEEDLES NOT INCLUDED

GSK

Havrix

Made in Belgium

©2023 the GSK group of companies or its licensor.

Rev. 10/23

515894